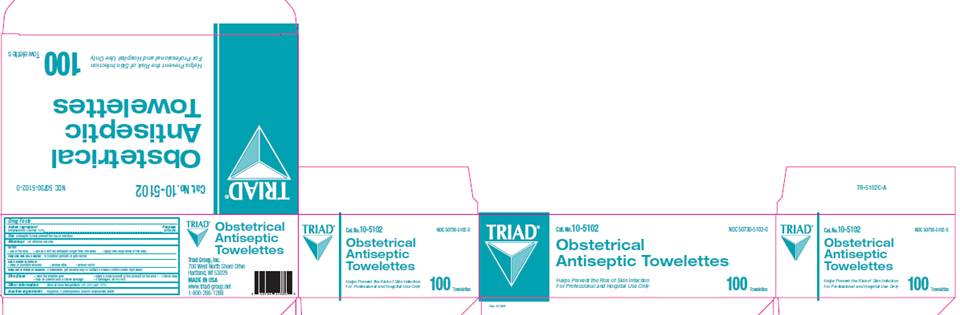 DRUG LABEL: OB Towelette
NDC: 50730-5102 | Form: SOLUTION
Manufacturer: H and P Industries, Inc. dba Triad Group
Category: otc | Type: HUMAN OTC DRUG LABEL
Date: 20091201

ACTIVE INGREDIENTS: benzalkonium chloride .004 mL/1 1
INACTIVE INGREDIENTS: sodium bicarbonate; water

DRUG FACTS

ACTIVE INGREDIENT

Benzalkonium chloride .4%

PURPOSE

Antiseptic

USE

Antiseptic to help prevent the risk of infection

WARNINGS

For external use only.

Do not

- use in the eyes
- use as a first aid antiseptic longer than one week
- apply over large areas of the body

Ask a doctor in case of

- deep or puncture wounds
- animal bites
- serious burns

Stop use and ask a doctor

if condition persists or gets worse

Keep out of reach of children

If swallowed, get medical help or contact a Poison Control Center right away.

DIRECTIONS

- clean the affected area
- apply a small amount of this product to the area 1-3 times daily
- may be covered with a sterile bandage
- if bandaged, let dry first

INACTIVE INGREDIENTS

fragrance, o-phenylphenol, sodium bicarbonate, water

CARTON INFORMATION

TRIAD
Cat. No. 10-5102
NDC 50730-5102-0
Obstetrical Antiseptic Towelettes
Helps prevent the risk of skin infections
For Professional and Hospital Use Only
100 towelettes